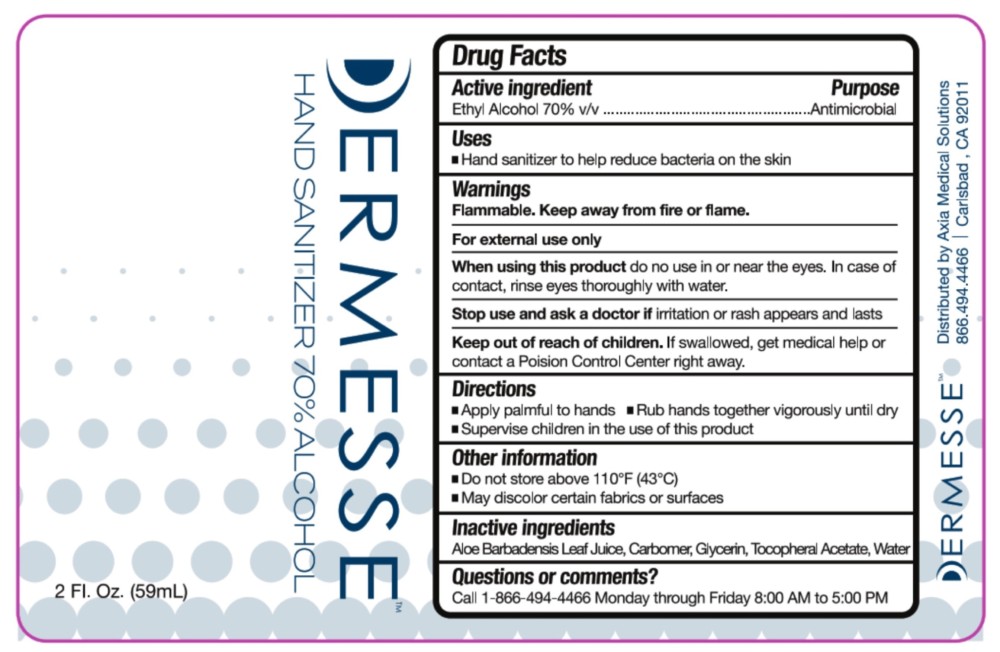 DRUG LABEL: Dermesse Hand Sanitizer Gel
NDC: 68723-200 | Form: GEL
Manufacturer: Axia Medical Solutions, LLC
Category: otc | Type: HUMAN OTC DRUG LABEL
Date: 20211222

ACTIVE INGREDIENTS: ALCOHOL 70 mL/100 mL
INACTIVE INGREDIENTS: ALOE VERA LEAF; CARBOMER 940; GLYCERIN; .ALPHA.-TOCOPHEROL ACETATE; WATER

Dermesse Hand Sanitizer

Active Ingredient:

Ethyl Alcohol

Purpose

Antimicrobial

USES:

Hand sanitizer to help reduce bacteria on the skin

WARNINGS:

Flammable. Keep away from fire or flame. For external use only.

When using the product:

• Do not use in or near the eyes. In case of contact, rinse eyes thoroughly with water.

Stop use and ask a doctor if:

Irritation or rash appears and lasts.

Keep out of reach of children.

If swallowed get medical help or contact a Poison Control Center right away.

DIRECTIONS:

- Apply palmful to hands
- Rub hands together vigorously until dry
- Supervise children in the use of this product

Inactive Ingredients:

Aloe Barbadensis Leaf Juice, Carbomer, Glycerin, Tocopheryl Acetate, Water

OTHER INFORMATION:

• Do not store above 110oF (43oC)

- May discolor certain fabrics or surfaces

Questions?:

866-494-4466, Mon-Fri 8:00AM-5:00PM

Dist. By Axia Medical Solutions, 2105 Camino Vida Roble, Carlsbad, Ca. 92011